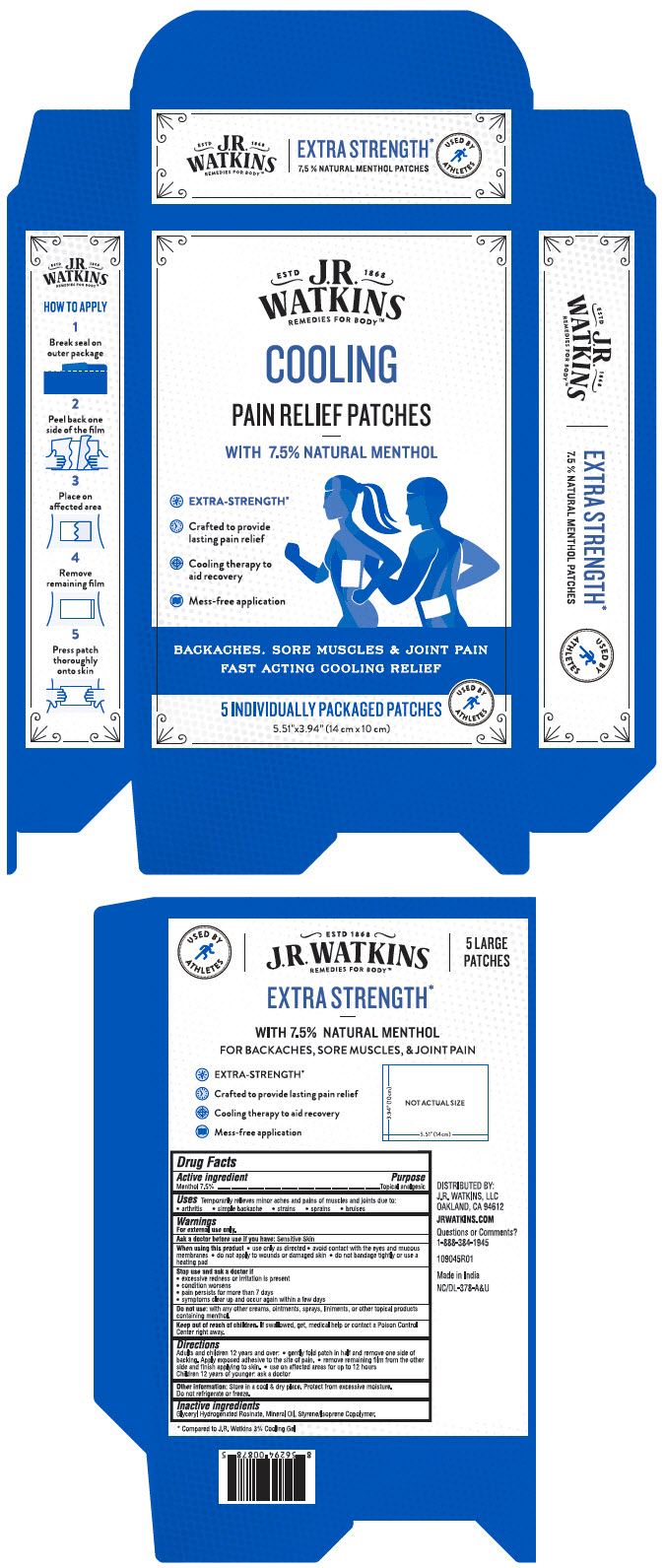 DRUG LABEL: Pain Relief
NDC: 72342-100 | Form: PATCH
Manufacturer: J.R. Watkins, LLC.
Category: otc | Type: HUMAN OTC DRUG LABEL
Date: 20240320

ACTIVE INGREDIENTS: MENTHOL, UNSPECIFIED FORM 105 mg/1 1
INACTIVE INGREDIENTS: GLYCERYL ROSINATE; MINERAL OIL; STYRENE/ISOPRENE/STYRENE BLOCK COPOLYMER

Pain Relief Patch
Cooling, Extra Strength

Drug Facts

Active Ingredient

Menthol 7.5%

Purpose

Topical Analgesic

Uses

Temporary relieves minor aches and pains of muscles and joints due to:

- arthritis
- simple backache
- strains
- sprains
- bruises

Warnings

For external use only.

Ask a doctor before use if you have

Sensitive Skin

When using this product

- use only as directed
- avoid contact with the eyes and mucous membranes
- do not apply to wounds or damaged skin
- do not bandage tightly or use a heating pad

Stop use and ask a doctor if

- excessive redness or irritation is present
- condition worsens
- pain persist for more than 7 days
- symptoms clear up and occur again within a few days

Do not use

- with any other creams, ointments, sprays, liniments, or other topical products containing menthol

Keep out of reach of children. If swallowed, get medical help or contact a Poison Control Center right away.

Directions

Adults and children 12 years and over:

- gently fold patch in half and remove one side of backing. Apply exposed adhesive to the site of pain.
- remove remaining film from the other side and finish applying to skin
- use on affected areas for up to 12 hours. Children 12 years of younger: ask a doctor

Other information

- Store in a cool & dry place. Protect from excessive moisture. Do no refrigerate or freeze.

Inactive ingredients

Glyceryl Hydrogenated Rosinate, Mineral Oil, Styrene/Isoprene Copolymer

Questions or Comments?

J.R WATKINS, LLC
OAKLAND, CA 94612
1-888-384-1945

PRINCIPAL DISPLAY PANEL - 5 Patch Box

ESTD
1868
J.R.
WATKINS
REMEDIES FOR BODY™

COOLING

PAIN RELIEF PATCHES

WITH 7.5% NATURAL MENTHOL

EXTRA-STRENGTH*

Crafted to provide
lasting pain relief

Cooling therapy to
aid recovery

Mess-free application

BACKACHES, SORE MUSCLES & JOINT PAIN
FAST ACTING COOLING RELIEF

5 INDIVIDUALLY PACKAGED PATCHES

USED BY
ATHLETES

5.51"x3.94" (14 cm x 10 cm)